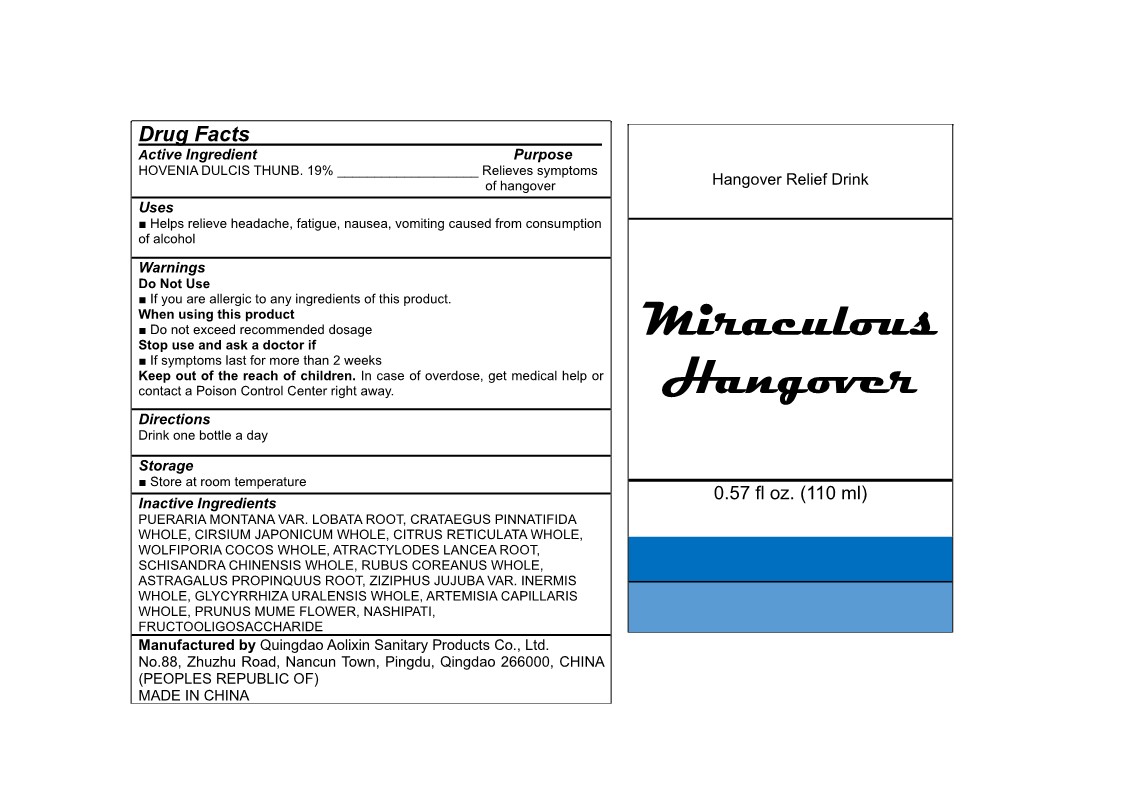 DRUG LABEL: Miraculous Hangover
NDC: 82672-301 | Form: LIQUID
Manufacturer: Qingdao Aolixin Sanitary Products Co., Ltd.
Category: otc | Type: HUMAN OTC DRUG LABEL
Date: 20220414

ACTIVE INGREDIENTS: HOVENIA DULCIS WHOLE 19 g/100 mL
INACTIVE INGREDIENTS: ATRACTYLODES LANCEA ROOT; GLYCYRRHIZA URALENSIS WHOLE; NASHIPATI; CRATAEGUS PINNATIFIDA WHOLE; ASTRAGALUS PROPINQUUS ROOT; CIRSIUM JAPONICUM; RUBUS COREANUS WHOLE; ZIZIPHUS JUJUBA VAR. INERMIS WHOLE; PUERARIA MONTANA VAR. LOBATA ROOT; CITRUS RETICULATA WHOLE; SCHISANDRA CHINENSIS WHOLE; ARTEMISIA CAPILLARIS WHOLE; WOLFIPORIA COCOS WHOLE; PRUNUS MUME FLOWER

Miraculous Hangover 82672-301

Active Ingredient

HOVENIA DULCIS THUNB. 19%

Purpose

Relieves symptoms of hangover

Uses

Helps relieve headache, fatigue, nausea, vomiting caused from consumption of alcohol

Do Not Use

If you are allergic to any ingredients of this product.

When Using This Product

Do not exceed recommended dosage

Stop us and ask a doctor if

symptoms last for more than 2 weeks

Keep out of the reach of children

Warnings

In case of overdose, get medical help or contact a Poison Control Center right away.

Directions

Drink one bottle a day.

Other Information

Store at room temperature.

Inactive Ingredients

PUERARIA MONTANA VAR. LOBATA ROOT, CRATAEGUS PINNATIFIDA WHOLE, CIRSIUM JAPONICUM WHOLE, CITRUS RETICULATA WHOLE, WOLFIPORIA COCOS WHOLE, ATRACTYLODES LANCEA ROOT, SCHISANDRA CHINENSIS WHOLE, RUBUS COREANUS WHOLE, ASTRAGALUS PROPINQUUS ROOT, ZIZIPHUS JUJUBA VAR. INERMIS WHOLE, GLYCYRRHIZA URALENSIS WHOLE, ARTEMISIA CAPILLARIS WHOLE, PRUNUS MUME FLOWER, NASHIPATI, FRUCTOOLIGOSACCHARIDE